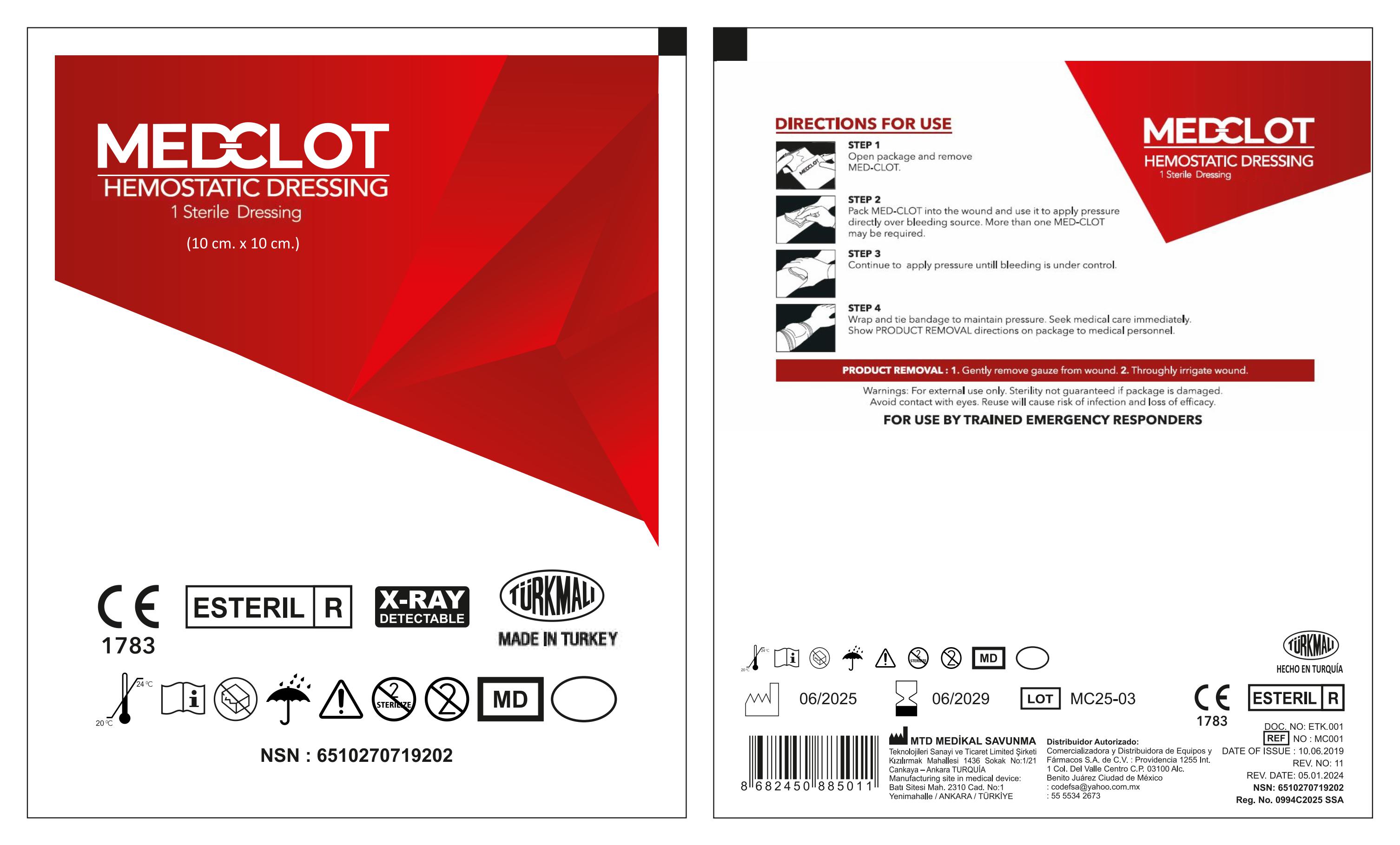 DRUG LABEL: MEDCLOT Hemostatic Dressing 10 cm x 10 cm
NDC: 85925-101 | Form: DRESSING
Manufacturer: Comercializadora y Distribuidora de Equipos y Fármacos, S.A. de C.V.
Category: otc | Type: HUMAN OTC DRUG LABEL
Date: 20250728

ACTIVE INGREDIENTS: CARBOXYMETHYLCELLULOSE 0.002 g/100 mL
INACTIVE INGREDIENTS: WATER

This is a HEMOSTATIC DRESSING - Sterile Dressing 10 cm x 10 cm

ACTIVE INGREDIENT

CarboxymethylCellulose

PURPOSE

Emergecy bleeding control.

For use by trained emergency responders.

INDICATIONS AND USAGE

1. Open package and remove MED-CLOT.

2. Pack MED-CLOT into the wound and use it to apply pressure directly over bleeding source. More than one MED-CLOT may be required.

3. Continue to apply pressure untill bleeding is under control.

4. Wrap and tie bandage to maintain pressure. Seek medical care immediately. Show PRODUCT REMOVAL directions on package to medical personnel.

WARNINGS

For external use only.

Sterility not guaranteed if package is damaged.

Avoid contact with eyes.

Reuse will cause risk of infection and loss of efficacy.

DOSAGE AND ADMINISTRATION

More than one MED-CLOT may be required.

Do not use if package is damaged.

WHEN USING

Reuse will cause risk of infection and loss of efficacy.

Keep out of reach of children.

Avoid contact with eyes.

STORAGE AND HANDLING

Keep at room temperature.

INACTIVE INGREDIENT

Purified water (standard ISO 13959:2014)

PACKAGE LABEL

85925-101-01